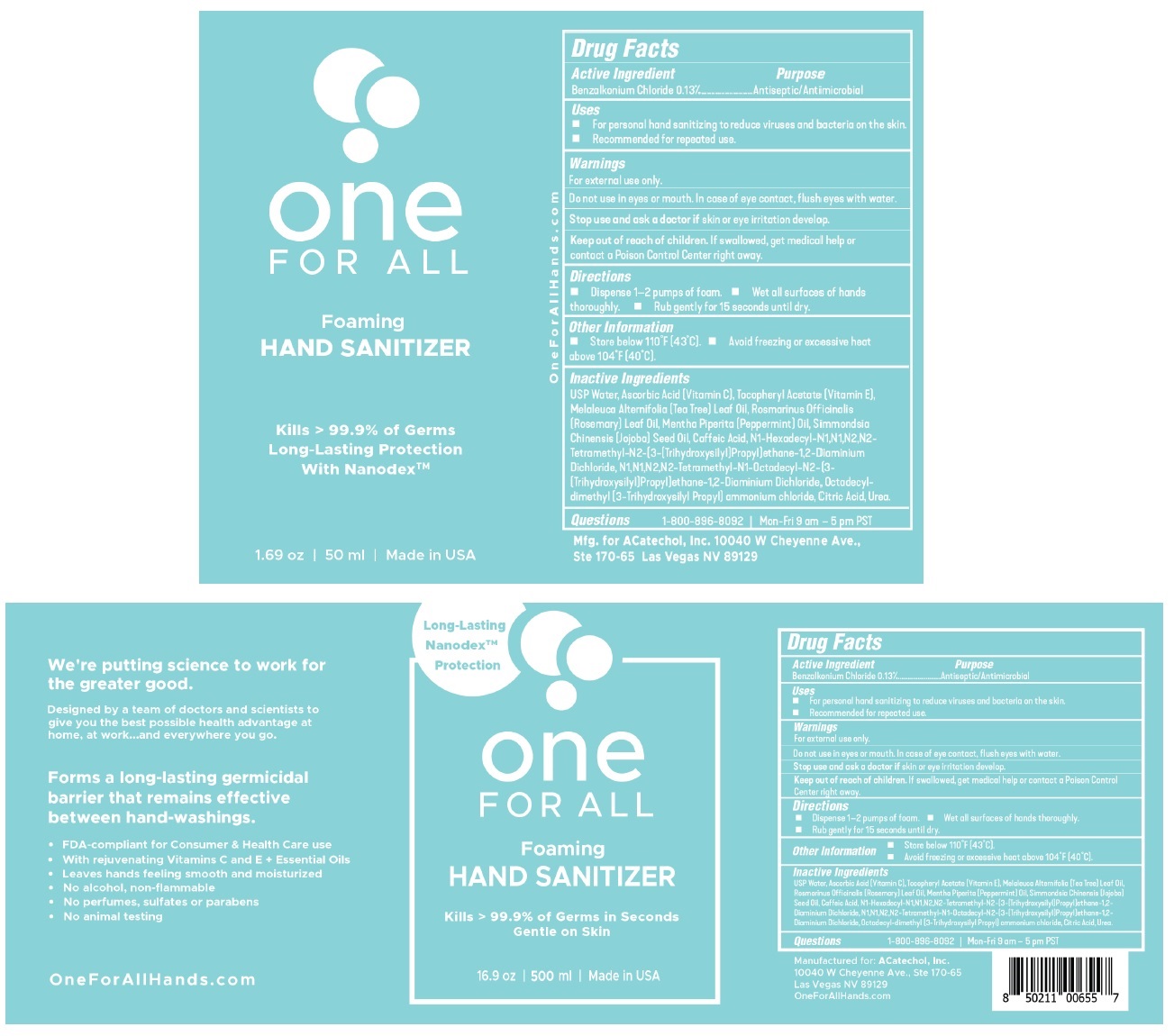 DRUG LABEL: One FOR ALL HAND SANITIZER
NDC: 80287-013 | Form: LIQUID
Manufacturer: Acatechol, Inc.
Category: otc | Type: HUMAN OTC DRUG LABEL
Date: 20210901

ACTIVE INGREDIENTS: BENZALKONIUM CHLORIDE 0.13 g/100 mL
INACTIVE INGREDIENTS: WATER; ASCORBIC ACID; .ALPHA.-TOCOPHEROL; TEA TREE OIL; ROSEMARY OIL; PEPPERMINT OIL; JOJOBA OIL; CAFFEIC ACID; N1-HEXADECYL-N1,N1,N2,N2-TETRAMETHYL-N2-(3-(TRIHYDROXYSILYL)PROPYL)ETHANE-1,2-DIAMINIUM DICHLORIDE; N1,N1,N2,N2-TETRAMETHYL-N1-OCTADECYL-N2-(3-(TRIHYDROXYSILYL)PROPYL)ETHANE-1,2-DIAMINIUM DICHLORIDE; OCTADECYLDIMETHYL(3-TRIHYDROXYSILYLPROPYL)AMMONIUM CHLORIDE; CITRIC ACID MONOHYDRATE; UREA

one FOR ALL HAND SANITIZER

Active Ingredient

Benzalkonium Chloride 0.13%

Purpose

Antiseptic/Antimicrobial

Uses

• For personal hand sanitizing to reduce viruses and bacteria on the skin.

• Recommended for repeated use.

Warnings

For external use only.

Do not use in eyes or mouth. In case of eye contact, flush eyes with water.

Stop use and ask a doctor if skin or eye irritation develop.

Keep out of reach of children. If swallowed, get medical help or contact a Poison Control Center right away.

Directions

• Dispense 1–2 pumps of foam.
• Wet all surfaces of hands thoroughly.
• Rub gently for 15 seconds until dry.

Other Information

• Store below 110°F (43°C).
• Avoid freezing or excessive heat above 104°F (40°C).

Inactive Ingredients

USP Water, Ascorbic Acid (Vitamin C), Tocopheryl Acetate (Vitamin E), Melaleuca Alternifolia (Tea Tree) Leaf Oil, Rosmarinus Officinalis (Rosemary) Leaf Oil, Mentha Piperita (Peppermint) Oil, Simmondsia Chinensis (Jojoba) Seed Oil, Caffeic Acid, N1-Hexadecyl-N1,N1,N2,N2-Tetramethyl-N2-(3-(Trihydroxysilyl)Propyl)ethane-1,2-Diaminium Dichloride, N1,N1,N2,N2-Tetramethyl-N1-Octadecyl-N2-(3-(Trihydroxysilyl)Propyl)ethane-1,2-Diaminium Dichloride, Octadecyl-dimethyl (3-Trihydroxysilyl Propyl) ammonium chloride, Citric Acid, Urea.

Questions

1-800-896-8092 | Mon-Fri 9 am – 5 pm PST

Long-Lasting Nanodex™ Protection

Kills > 99.99% of Germs in Seconds

Gentle on Skin

Made in USA

We're putting science to work for the greater good.

Designed by a team of doctors and scientists to give you the best possible health advantage at home, at work...and everywhere you go.

Forms a long-lasting germicidal barrier that remains effective between hand-washings.

• FDA-compliant for Consumer & Health Care use

• With rejuvenating Vitamins C and E + Essential Oils

• Leaves hands feeling smooth and moisturized

• No alcohol, non-flammable

• No perfumes, sulfates or parabens

• No animal testing

Manufactured for: ACatechol, Inc.

10040 W Cheyenne Ave., Ste 170-65

Las Vegas NV 89129

OneForAllHands.com